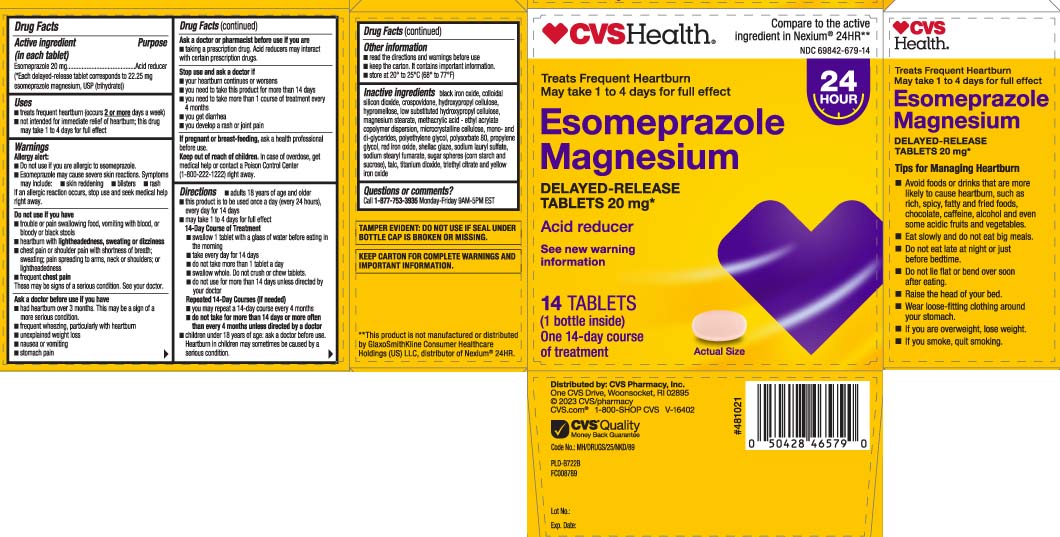 DRUG LABEL: Acid Reducer
NDC: 69842-679 | Form: TABLET, DELAYED RELEASE
Manufacturer: CVS Pharmacy
Category: otc | Type: HUMAN OTC DRUG LABEL
Date: 20260121

ACTIVE INGREDIENTS: ESOMEPRAZOLE MAGNESIUM 20 mg/1 1
INACTIVE INGREDIENTS: SILICON DIOXIDE; HYPROMELLOSE, UNSPECIFIED; GLYCERYL MONO AND DIPALMITOSTEARATE; MAGNESIUM STEARATE; METHACRYLIC ACID AND ETHYL ACRYLATE COPOLYMER; POLYSORBATE 80; SODIUM LAURYL SULFATE; SUCROSE; STARCH, CORN; TALC; TITANIUM DIOXIDE; TRIETHYL CITRATE; CROSPOVIDONE; HYDROXYPROPYL CELLULOSE, UNSPECIFIED; HYDROXYPROPYL CELLULOSE, LOW SUBSTITUTED; MICROCRYSTALLINE CELLULOSE; POLYETHYLENE GLYCOL, UNSPECIFIED; PROPYLENE GLYCOL; SHELLAC; SODIUM STEARYL FUMARATE; FERROSOFERRIC OXIDE; FERRIC OXIDE RED; FERRIC OXIDE YELLOW

Esomeprazole Magnesium Delayed-Release Capsules 20 mg - Actavis

Active ingredient (in each tablet)

Esomeprazole 20 mg
(*Each delayed-release tablet corresponds to 22.25 mg esomeprazole magnesium, USP trihydrate)

Purpose

Acid reducer

Uses

- treats frequent heartburn (occurs 2 or more days a week)
- not intended for immediate relief of heartburn; this drug may take 1 to 4 days for full effect

Warnings

Allergy alert:

- Do not use if you are allergic to esomeprazole.
- Esomeprazole may cause severe skin reactions. Symptoms may include:
- skin reddening
- blisters
- rash

If an allergic reaction occurs, stop use and seek medical help right away.

Do not use if you have:

- trouble or pain swallowing food, vomiting with blood, or bloody or black stools
- heartburn with lightheadedness, sweating or dizziness
- chest pain or shoulder pain with shortness of breath; sweating; pain spreading to arms, neck or shoulders; or lightheadedness
- frequent chest pain

These may be signs of a serious condition. See your doctor.

Ask a doctor before use if you have

- had heartburn over 3 months. This may be a sign of a more serious condition.
- frequent wheezing, particularly with heartburn
- unexplained weight loss
- nausea or vomiting
- stomach pain

Ask a doctor or pharmacist before use if you are taking

- taking a prescription drug. Acid reducers may interact with certain prescription drugs.

Stop use and ask a doctor if

- your heartburn continues or worsens
- you need to take this product for more than 14 days
- you need to take more than 1 course of treatment every 4 months
- you get diarrhea
- you develop a rash or joint pain

If pregnant or breast-feeding,

ask a health professional before use.

Keep out of reach of children.

In case of overdose, get medical help or contact a Poison Control Center (1-800-222-1222) right away.

Directions

- adults 18 years of age and older
- this product is to be used once a day (every 24 hours), every day for 14 days
- may take 1 to 4 days for full effect

14-Day Course of Treatment
• swallow 1 tablet with a glass of water before eating in the morning
• take every day for 14 days
• do not take more than 1 tablet a day
• swallow whole. Do not crush or chew capsules.
• do not use for more than 14 days unless directed by your doctor

Repeated 14-Day Courses (if needed)
• you may repeat a 14-day course every 4 months
• do not take for more than 14 days or more often than every 4 months unless directed by a doctor

- children under 18 years of age: ask a doctor before use. Heartburn in children may sometimes be caused by a serious condition.

Other information

- read the directions and warnings before us
- keep the carton. It contains important information.
- store at 20° to 25°C (68° to 77°F)

Inactive ingredients

black iron oxide, colloidal silicon dioxide, crospovidone, hydroxypropyl cellulose, hypromellose, low substituted hydroxypropyl cellulose, magnesium stearate, methacrylic acid - ethyl acrylate copolymer dispersion, microcrystalline cellulose, mono-and di-glycerides, polyethylene glycol, polysorbate 80, propylene glycol, red iron oxide, shellac glaze, sodium lauryl sulfate, sodium stearyl fumarate, sugar spheres (corn starch and sucrose), talc, titanium dioxide, triethyl citrate and yellow iron oxide

Questions or comments?

Call 1-877-753-3935 Monday-Friday 9AM-5PM EST

Principal Display Panel

Compare to the active ingredient in Nexium® 24R†

Treats Frequent Heartburn

May take 1 to 4 days for full effect

Esomeprazole Magnesium

DELAYED-RELEASE TABLETS 20 mg*

Acid reducer

See new warning information

TABLET

One 14-day course of treatment

**This product is not manufactured or distributed by GlaxoSmithKline Consumer Healthcare Holdings (US) LLC, distributor of Nexium® 24HR.

TAMPER EVIDENT: DO NOT USE IF SEAL UNDER BOTTLE CAP BROKEN OR MISSING.

KEEP CARTON FOR COMPLETE WARNINGS AND PRODUCT INFORMATION.

Distributed by: CVS Pharmacy, Inc.

One CVS Drive, Woonsocket, RI 02895

Package label

CVS HEALTH Acid Reducer